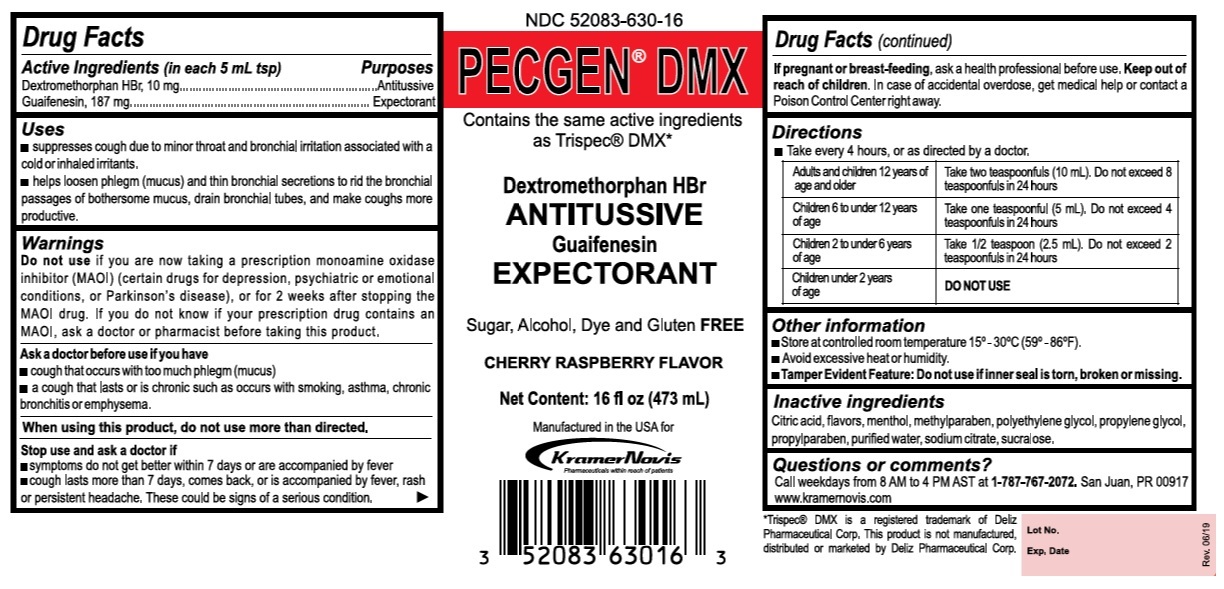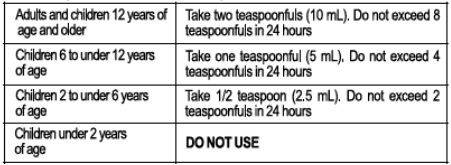 DRUG LABEL: PECGEN DMX
NDC: 52083-630 | Form: SOLUTION
Manufacturer: KRAMER NOVIS
Category: otc | Type: HUMAN OTC DRUG LABEL
Date: 20251114

ACTIVE INGREDIENTS: DEXTROMETHORPHAN HYDROBROMIDE 10 mg/5 mL; GUAIFENESIN 187 mg/5 mL
INACTIVE INGREDIENTS: CITRIC ACID MONOHYDRATE; MENTHOL, UNSPECIFIED FORM; METHYLPARABEN; POLYETHYLENE GLYCOL 1000; PROPYLENE GLYCOL; PROPYLPARABEN; WATER; SODIUM CITRATE, UNSPECIFIED FORM; SUCRALOSE

PECGEN® DMX

Active Ingredients (in each 5 mL tsp)

Dextromethorphan HBr, 10 mg

Guaifenesin, 187 mg

Purposes

Antitussive

Expectorant

Uses

• suppresses cough due to minor throat and bronchial irritation associated with a cold or inhaled irritants.

• helps loosen phlegm (mucus) and thin bronchial secretions to rid the bronchial passages of bothersome mucus, drain bronchial tubes, and make coughs more productive.

Warnings

Do not use if you are now taking a prescription monoamine oxidase inhibitor (MAOI) (certain drugs for depression, psychiatric or emotional conditions, or Parkinson's disease), or for 2 weeks after stopping the MAOI drug. If you do not know if your prescription drug contains an MAOI, ask a doctor or pharmacist before taking this product.

Ask a doctor before use if you have
• cough that occurs with too much phlegm (mucus)
• a cough that lasts or is chronic such as occurs with smoking, asthma, chronic bronchitis or emphysema.

When using this product, do not use more than directed.

Stop use and ask a doctor if
• symptoms do not get better within 7 days or are accompanied by fever
• cough lasts more than 7 days, comes back, or is accompanied by fever, rash or persistent headache. These could be signs of a serious condition.

If pregnant or breast-feeding, ask a health professional before use.

Keep out of reach of children. In case of accidental overdose, get medical help or contact a Poison Control Center right away.

Directions

Take every 4 hours, or as directed by a doctor.

Inactive ingredients

Citric acid, flavors, menthol, methylparaben, polyethylene glycol, propylene glycol, propylparaben, purified water, sodium citrate, sucralose.

Other information

• Store at controlled room temperature 15°-30°C (59°-86°F).
• Avoid excessive heat or humidity.
• Tamper Evident Feature: Do not use if inner seal is torn, broken or missing.

Questions or comments?

Call weekdays from 8 AM to 4 PM AST at 1-787-767-2072. San Juan, PR 00917
www.kramernovis.com

Contains the same active ingredients as Trispec® DMX*

Sugar, Alcohol, Dye and Gluten FREE

CHERRY RASPBERRY FLAVOR

Manufactured in the USA for Kramer Novis

*Trispec® DMX is a registered trademark of Deliz Pharmaceutical Corp. This product is not manufactured, distributed or marketed by Deliz Pharmaceutical Corp.